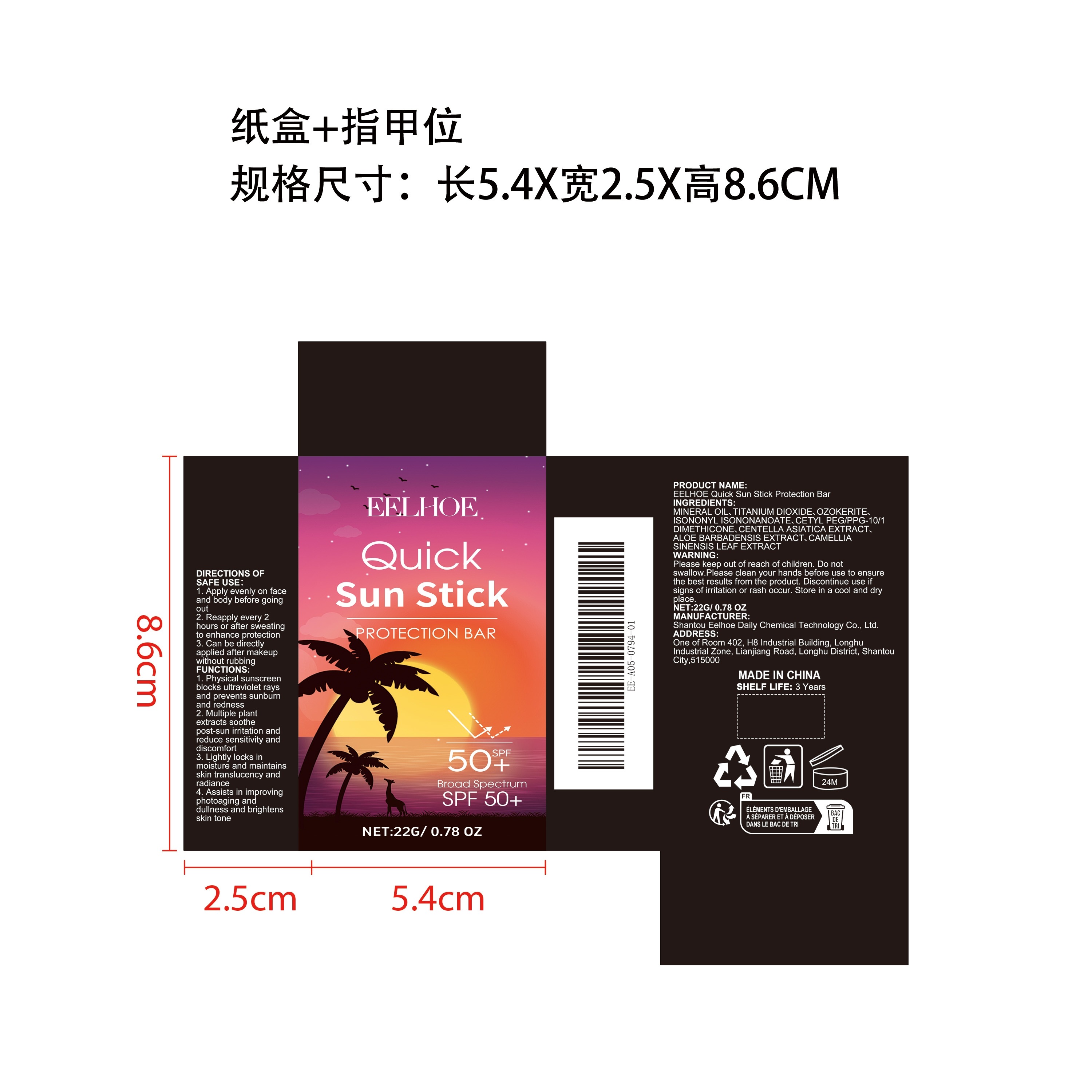 DRUG LABEL: EELHOE Quick Sun Stick Protection Bar
NDC: 85064-009 | Form: STICK
Manufacturer: Shantou Eelhoe Daily Chemical Technology Co., Ltd.
Category: otc | Type: HUMAN OTC DRUG LABEL
Date: 20251127

ACTIVE INGREDIENTS: CENTELLA ASIATICA LEAF 0.0044 mg/22 mg; CAMELLIA SINENSIS LEAF 0.0044 mg/22 mg; ALOE BARBADENSIS LEAF 0.0044 mg/22 mg
INACTIVE INGREDIENTS: ISONONYL ISONONANOATE 2.2 mg/22 mg; CERESIN 4.4 mg/22 mg; MINERAL OIL 9.1168 mg/22 mg; CETYL PEG/PPG-10/1 DIMETHICONE (HLB 2) 0.77 mg/22 mg; TITANIUM DIOXIDE 5.5 mg/22 mg

ACTIVE INGREDIENT

CENTELLA ASIATICA EXTRACT、ALOE BARBADENSIS EXTRACT、CAMELLIA SINENSIS LEAF EXTRACT

PURPOSE

1. Physical sunscreen blocks ultraviolet rays and prevents sunburn and redness

2. Multiple plant extracts soothe post-sun irritation and reduce sensitivity and discomfort

3. Lightly locks in moisture and maintains skin translucency and radiance

4. Assists in improving photoaging and dullness and brightens skin tone

WHEN USING

1. Apply evenly on face and body before going out

2. Reapply every 2 hours or after sweating to enhance protection

3. Can be directly applied after makeup without rubbing

WARNINGS

Please keep out of reach of children. Do not swallow.Please clean your hands before use to ensure the best results from the product. Discontinue use if signs of irritation or rash occur. Store in a cool and dry place.

KEEP OUT OF REACH OF CHILDREN

Please keep out of reach of children. Do not swallow.

STOP USE

Discontinue use if signs of irritation or rash occur.

STORAGE AND HANDLING

Store in a cool and dry place.

INACTIVE INGREDIENT

MINERAL OIL、TITANIUM DIOXIDE、OZOKERITE、ISONONYL ISONONANOATE、CETYL PEG/PPG-10/1 DIMETHICONE